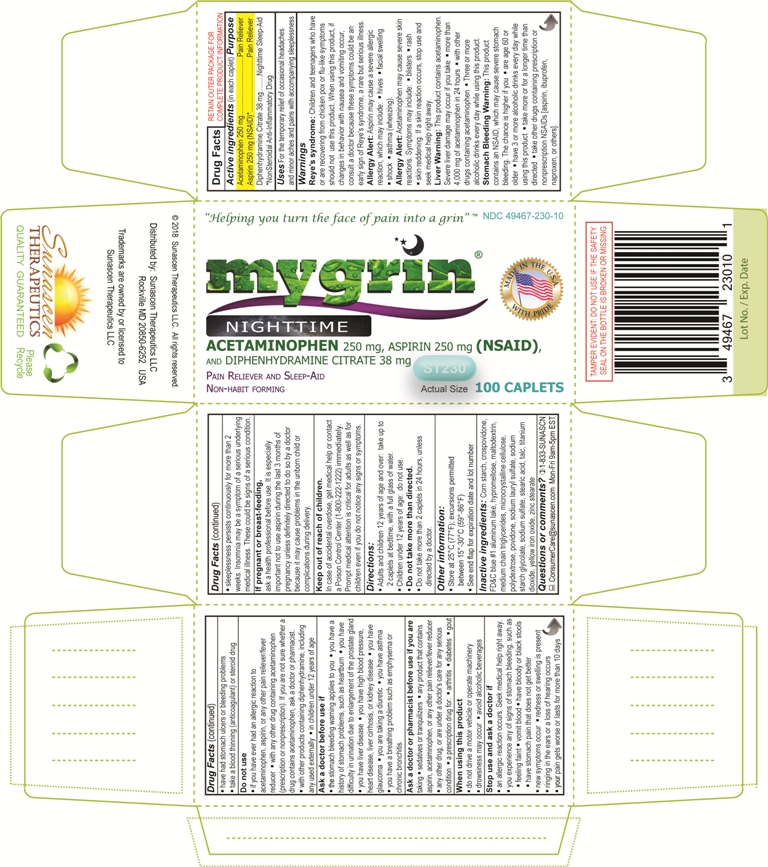 DRUG LABEL: MYGRIN Nighttime
NDC: 49467-230 | Form: TABLET, FILM COATED
Manufacturer: Sunascen Therapeutics LLC
Category: otc | Type: HUMAN OTC DRUG LABEL
Date: 20230209

ACTIVE INGREDIENTS: ACETAMINOPHEN 250 mg/1 1; ASPIRIN 250 mg/1 1; DIPHENHYDRAMINE CITRATE 38 mg/1 1
INACTIVE INGREDIENTS: STARCH, CORN; CROSPOVIDONE, UNSPECIFIED; FD&C BLUE NO. 1; HYPROMELLOSE, UNSPECIFIED; MALTODEXTRIN; MEDIUM-CHAIN TRIGLYCERIDES; MICROCRYSTALLINE CELLULOSE; POLYDEXTROSE; POVIDONE, UNSPECIFIED; SODIUM LAURYL SULFATE; SODIUM STARCH GLYCOLATE TYPE A POTATO; SODIUM SULFATE; STEARIC ACID; TALC; TITANIUM DIOXIDE; FERRIC OXIDE YELLOW; ZINC STEARATE

MYGRIN® Nighttime (Acetaminophen, Aspirin (NSAID), and Diphenhydramine Citrate), Caplets

ACTIVE INGREDIENTS (In each caplet)

Acetaminophen 250 mg
Aspirin 250 mg (NSAID)*
Diphenhydramine citrate 38 mg
*NonSteroidal Anti-Inflammatory Drug

PURPOSE

Pain reliever
Pain reliever
Nighttime sleep-aid

INDICATIONS AND USAGE

For the temporary relief of occasional headaches, and minor aches and pains, with accompanying sleeplessness

WARNINGS

Reye's Syndrome

Children and teenagers who have or are recovering from chicken pox or flu-like symptoms should not use this product. When using this product, if changes in behavior with nausea and vomiting occur, consult a doctor because these symptoms could be an early sign of Reye's syndrome, a rare but serious illness.

Allergy Alert (Aspirin)

Aspirin may cause a severe allergic reaction, which may include the following,

- Hives
- Facial swelling
- Shock
- Asthma (Wheezing)

Allergy Alert (Acetaminophen)

Acetaminophen may cause severe skin reactions. Symptoms may include the following,

- Blisters
- Rash
- Skin reddening

If a skin reaction does occur, stop use and seek medical help right away.

Liver Warning

This product contains acetaminophen. Severe liver damage may occur if you take the following,

- More than 4,000 mg of acetaminophen in 24 hours, which is the maximum daily amount
- With other drugs containing acetaminophen
- Three or more alcoholic drinks every day while using this product

Stomach Bleeding Warning

This product contains an NSAID, which may cause severe stomach bleeding. The chance of severe stomach bleeding is higher if you

- Are age 60 or older
- Have 3 or more alcoholic drinks every day while using this product
- Take more than directed, or for a longer time than directed
- Take other drugs containing prescription or nonprescription NSAIDs [aspirin, ibuprofen, naproxen or others]
- Have had stomach ulcers or bleeding problems
- Take a blood thinning (anticoagulant) or steroid drug

Do not use this product in the following scenarios,

- If you ever had an allergic reaction to acetaminophen, aspirin, or any other pain reliever/fever reducer
- With any other drug containing acetaminophen (prescription or non prescription). If you are not sure whether a drug contains acetaminophen, ask a doctor or pharmacist.
- With other products containing diphenhydramine, including any used externally
- In children under 12 years of age

Ask a doctor before using this product if,

- The stomach bleeding warning applies to you
- You have a history of stomach problems, such as heartburn
- You have difficulty in urination due to enlargement of the prostate gland
- You have liver disease
- You have high blood pressure, heart disease, liver cirrhosis or kidney disease
- You have glaucoma
- You are taking a diuretic
- You have asthma
- You have a breathing problem such as emphysema or chronic bronchitis

Ask a Doctor or a Pharmacist

Ask a doctor or pharmacist before using this product if you are taking the following,

- A prescription drug for:
  + Arthritis
  + Diabetes
  + Gout
- Sedatives or Tranquilizers
- Any product that contains aspirin, acetaminophen, or any other pain reliever/fever reducer
- Any other drug, or are under a doctor's care for any serious condition

When using this product,

- Do not drive a motor vehicle or operate machinery
- Drowsiness may occur
- Avoid alcoholic beverages

Stop Use and ask a Doctor

Stop use of this product and ask a Doctor in the event of the following,

- If an allergic reaction occurs. Seek medical help right away.
- You experience any of signs of stomach bleeding, such as
  + Feeling faint
  + Vomit blood
  + Have bloody or black stools
  + Have stomach pain that does not get better
- New symptoms occur
- Redness or swelling is present
- Ringing in the ears or loss of hearing occurs
- Your pain gets worse or lasts for more than 10 days
- Sleeplessness persists continuously for more than 2 weeks. Insomnia may be a symptom of a serious underlying medical illness.

These could be signs of a serious condition

Pregnancy and Nursing Mothers

If pregnant or breast-feeding ask a health professional before use. It is especially important not to use aspirin during the last 3 months of pregnancy unless definitely directed to do so by a doctor because it may cause problems in the unborn child or complications during delivery.

Keep out of reach of children

In case of an overdose, seek medical help right away or contact a Poison Control Center (1-800-222-1222) immediately. Prompt medical attention is critical for adults as well as for children even if you do not notice any signs or symptoms.

DOSAGE AND ADMINISTRATION (Directions)

Adults and children 12 years of age and over: take up to 2 caplets at bedtime, with a full glass of water.

- Do not take more than directed
- Do not take more than 2 caplets in 24 hours, unless directed by a doctor
- Do not use in children under 12 years of age

Keep out of reach of children. In case of an overdose, seek medical help right away or contact a Poison Control Center immediately.
Call Poison Control at 1-800-222-1222. Prompt medical attention is critical for adults as well as for children even if you do not notice any signs or symptoms.

STORAGE AND HANDLING

- Store at 25ºC (77ºF); Excursions permitted between 15º-30ºC (59º-86ºF)
- See end flap for expiration date and lot number

INACTIVE INGREDIENTS

Corn Starch, Crospovidone, FD&C Blue #1 Aluminum Lake, Hypromellose, Maltodextrin, Medium Chain Triglycerides, Microcrystalline Cellulose, Polydextrose, Sodium Lauryl Sulfate, Sodium Starch Glycolate, Sodium Sulfate, Stearic Acid, Talc, Titanium Dioxide, Yellow Iron Oxide, Zinc Stearate.

QUESTIONS OR COMMENTS?

Sunascen Therapeutics LLC
Call us toll free at 1-833-SUNASCN (786-2726) Mon-Fri 9am-5pm EST.
Email us at ConsumerCare@Sunascen.com
More information is available on our website at www.sunascen.com

PRINCIPAL DISPLAY PANEL

Sunascen Therapeutics LLC

NDC 49467-230-10

MYGRIN NIGHTTIME
ACETAMINOPHEN, 250 mg
ASPIRIN (NSAID), 250 mg
DIPHENHYDRAMINE CITRATE, 38 mg

Pain Reliever and Sleep-Aid
Non-habit forming

"Helping you turn the face of pain into a grin" ™

100 CAPLETS

TAMPER EVIDENT: DO NOT USE IF THE SAFETY SEAL UNDER CAP IS BROKEN OR MISSING

Distributed by: Sunascen Therapeutics LLC, Rockville MD 20850
© 2018 Sunascen Therapeutics LLC, All rights reserved.
Trademarks are owned by or licensed to Sunascen Therapeutics LLC

Sunascen Therapeutics LLC
Quality Guaranteed
Please Recycle